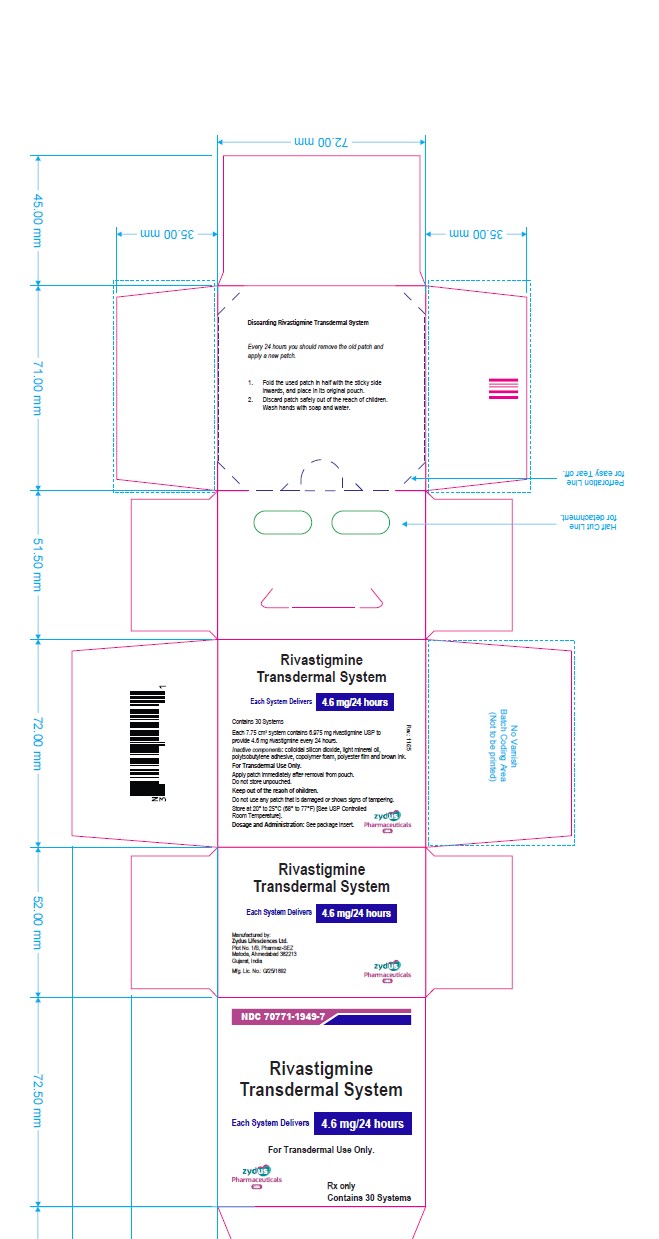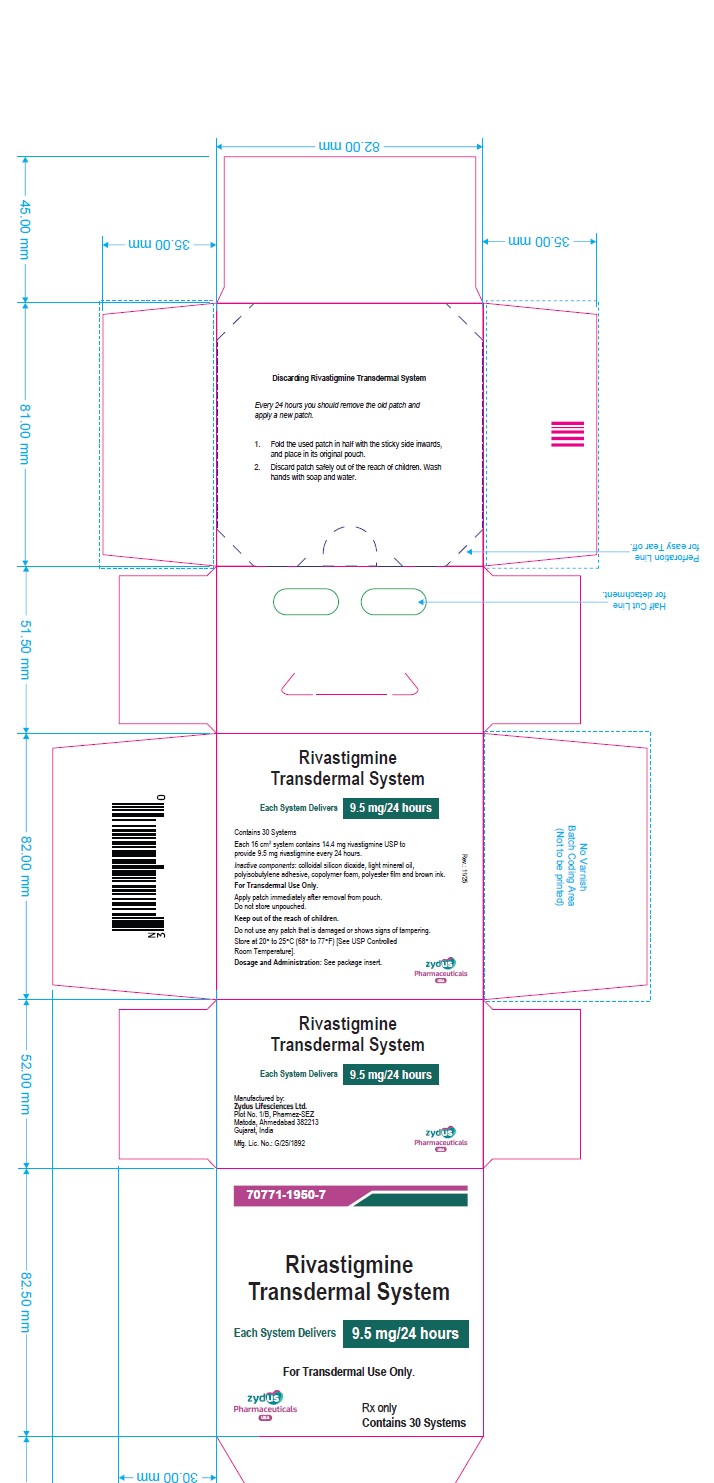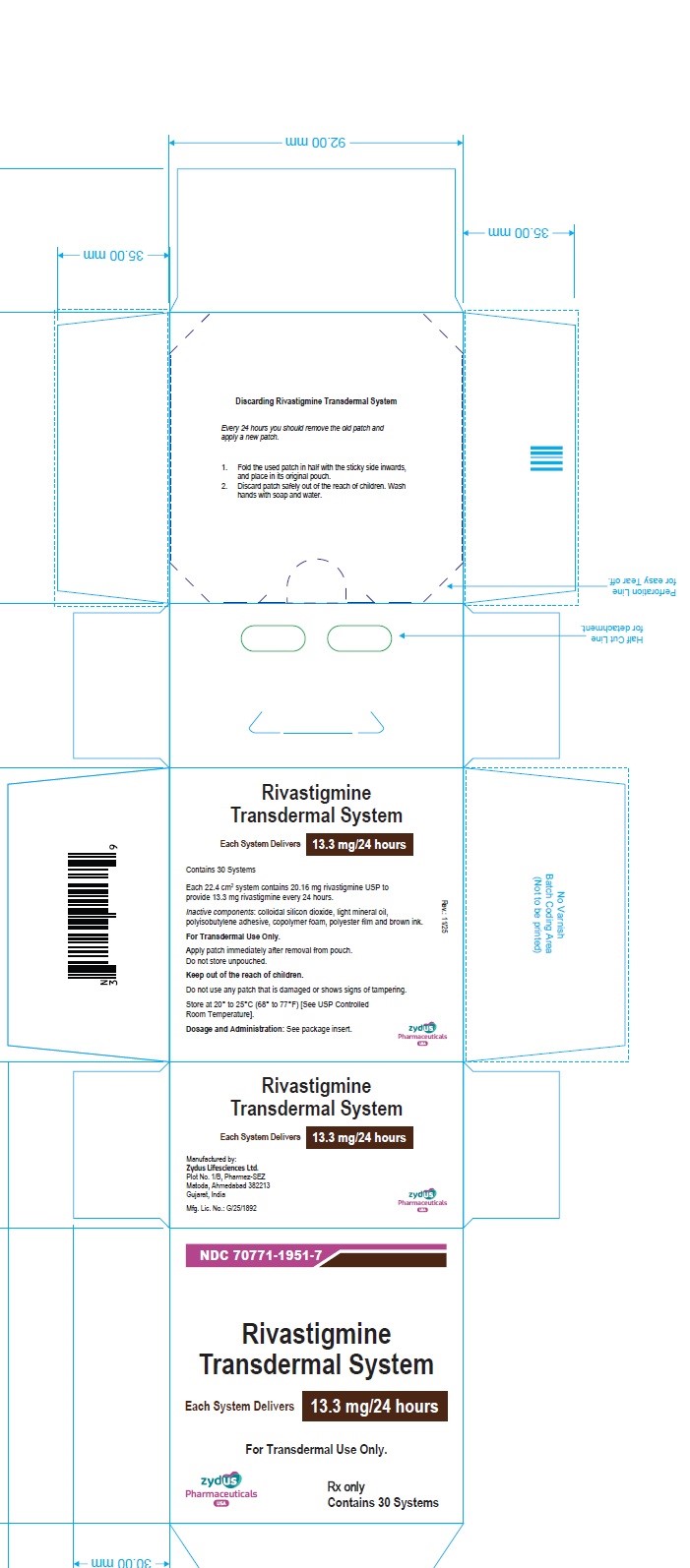 DRUG LABEL: Rivastigmine
NDC: 70771-1949 | Form: PATCH, EXTENDED RELEASE
Manufacturer: Zydus Lifesciences Limited
Category: prescription | Type: HUMAN PRESCRIPTION DRUG LABEL
Date: 20251117

ACTIVE INGREDIENTS: RIVASTIGMINE 4.6 mg/24 h
INACTIVE INGREDIENTS: SILICON DIOXIDE; LIGHT MINERAL OIL; POLYISOBUTYLENE (1100000 MW); POLYISOBUTYLENE (55000 MW)

Rivastigmine Transdermal System

PACKAGE LABEL.PRINCIPAL DISPLAY PANEL

Rx only

NDC 70771-1949-7

Rivastigmine

Transdermal System

Each System Delivers 4.6 mg/24 hours

For Transdermal Use Only.

Contains 30 systems

Rx only

NDC 70771-1950-7

Rivastigmine

Transdermal System

Each System Delivers 9.5 mg/24 hours

For Transdermal Use Only.

Contains 30 systems

Rx only

NDC 70771-1951-7

Rivastigmine

Transdermal System

Each System Delivers 13.3 mg/24 hours

For Transdermal Use Only.

Contains 30 systems